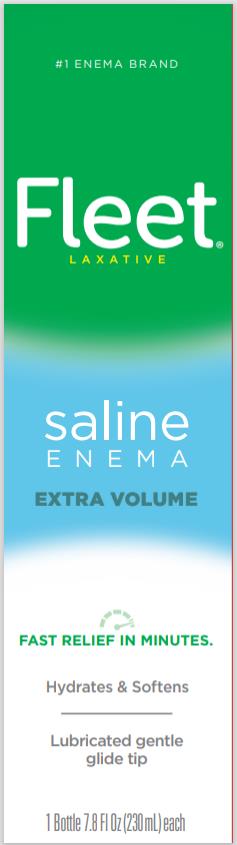 DRUG LABEL: Fleet
NDC: 0132-0078 | Form: ENEMA
Manufacturer: C.B. Fleet Company, Inc.
Category: otc | Type: HUMAN OTC DRUG LABEL
Date: 20240229

ACTIVE INGREDIENTS: SODIUM PHOSPHATE, DIBASIC, HEPTAHYDRATE 7 g/230 mL; sodium phosphate, monobasic 19 g/230 mL
INACTIVE INGREDIENTS: EDETATE DISODIUM; WATER; BENZALKONIUM CHLORIDE

Fleet Saline Enema Extra 0132-0078

Drug Facts

Purpose

(in each 197 mL delivered dose)

Monobasic sodium phosphate 19g ... Saline laxative

Dibasic sodium phosphate 7g ......... Saline laxative

Use

for relief of occasional constipation. This product usually produces a bowel movement in 1 to 5 minutes.

Warnings

For rectal use only.

Using more than one enema in 24 hours can be harmful.

Do not use

• for more than 3 days

• if you have kidney disease

• if you have heart problems

• if you are dehydrated

• when abdominal pain, nausea, or vomiting are present unless directed by a doctor

Ask a doctor before using this product if you

• are 55 years of age or older

• are on a sodium-restricted diet

• have a sudden change in bowel habits lasting more than 2 weeks

• already used a laxative for more than 1 week

Stop use and ask a doctor if you have

• rectal bleeding

• no bowel movement or no liquid comes out of the rectum after 30 minutes

• symptoms of dehydration [feeling thirsty, dizziness, vomiting, urinating less often than normal]

These symptoms may indicate a serious condition.

Keep out of reach of children.

If swallowed, get medical help or contact a Poison Control Center (1-800-222-1222) right away.

Directions

Single Daily Dosage (per 24 hours).

Do not use if taking another sodium phosphates product. Do not use more unless directed by a

doctor. See Warnings.

adults and children 12 and over | 1 bottle per day
children 2 to 11 years | use Fleet® Pedia-Lax® Enema
children under 2 years | DO NOT USE

If no urge is felt after 5 minutes of using, try to empty bowel. Call a doctor promptly if no liquid comes out of the rectum after 30 minutes because dehydration could occur.

Other information

• each 197 mL delivered dose contains: sodium 4.4 g

• additional liquids by mouth are recommended while taking this product

Inactive ingredients

benzalkonium chloride, disodium EDTA, purified water

Questions?

1-866-255-6960 or www.fleetlabs.com

PRINCIPAL DISPLAY PANEL

Fleet
Laxative
Saline
Enema
Extra Volume
1 Bottle 7.8 Fl Oz (230 mL) each